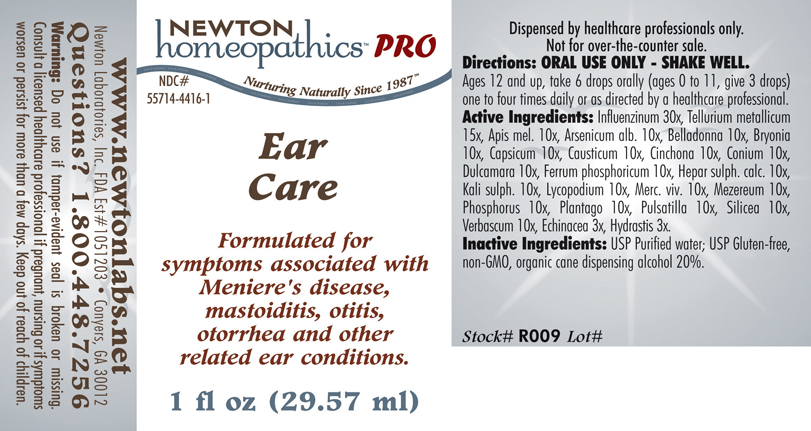 DRUG LABEL: Ear Care 
NDC: 55714-4416 | Form: LIQUID
Manufacturer: Newton Laboratories, Inc.
Category: homeopathic | Type: HUMAN PRESCRIPTION DRUG LABEL
Date: 20110601

ACTIVE INGREDIENTS: Influenza A Virus 30 [hp_X]/1 mL; Tellurium 15 [hp_X]/1 mL; Apis Mellifera 10 [hp_X]/1 mL; Arsenic Trioxide 10 [hp_X]/1 mL; Atropa Belladonna 10 [hp_X]/1 mL; Bryonia Alba Root 10 [hp_X]/1 mL; Capsicum 10 [hp_X]/1 mL; Causticum 10 [hp_X]/1 mL; Cinchona Officinalis Bark 10 [hp_X]/1 mL; Conium Maculatum Flowering Top 10 [hp_X]/1 mL; Solanum Dulcamara Stem 10 [hp_X]/1 mL; Ferrosoferric Phosphate 10 [hp_X]/1 mL; Calcium Sulfide 10 [hp_X]/1 mL; Potassium Sulfate 10 [hp_X]/1 mL; Lycopodium Clavatum Spore 10 [hp_X]/1 mL; Mercury 10 [hp_X]/1 mL; Daphne Mezereum Bark 10 [hp_X]/1 mL; Phosphorus 10 [hp_X]/1 mL; Plantago Major 10 [hp_X]/1 mL; Pulsatilla Vulgaris 10 [hp_X]/1 mL; Silicon Dioxide 10 [hp_X]/1 mL; Verbascum Thapsus 10 [hp_X]/1 mL; Echinacea, Unspecified 3 [hp_X]/1 mL; Goldenseal 3 [hp_X]/1 mL; Influenza B Virus 30 [hp_X]/1 mL
INACTIVE INGREDIENTS: Alcohol

Ear Care

INDICATIONS & USAGE SECTION

EAR CARE Formulated for symptoms associated with Meniere's disease, mastoiditis, otitis, otorrhea and other related ear conditions.

DOSAGE & ADMINISTRATION SECTION

Directions: ORAL USE ONLY - SHAKE WELL. Ages 12 and up, take 6 drops orally (ages 0 to 11, give 3 drops) one to four times daily or as directed by a healthcare professional.

ACTIVE INGREDIENT SECTION

Influenzinum 30x, Tellurium metallicum 15x, Apis mel. 10x, Arsenicum alb. 10x, Belladonna 10x, Bryonia 10x, Capsicum 10x, Causticum 10x, Cinchona 10x, Conium 10x, Dulcamara 10x, Ferrum phosphoricum 10x, Hepar sulph. calc. 10x, Kali sulph. 10x, Lycopodium 10x, Merc. viv. 10x, Mezereum 10x, Phosphorus 10x, Plantago 10x, Pulsatilla 10x, Silicea 10x, Verbascum 10x, Echinacea 3x, Hydrastis 3x.

INACTIVE INGREDIENT SECTION

Inactive Ingredients: USP Purified Water; USP Gluten-free, non-GMO, organic cane dispensing alcohol 20%.

QUESTIONS? SECTION

www.newtonlabs.net Newton Laboratories, Inc. FDA Est # 1051203 - Conyers, GA 30012
Questions? 1.800.448.7256

WARNINGS SECTION

Warning: Do not use if tamper- evident seal is broken or missing. Consult a licensed healthcare professional if pregnant, nursing or if symptoms worsen or persist for more than a few days. Keep out of reach of children.

PREGNANCY OR BREAST FEEDING SECTION

Consult a licensed healthcare professional if pregnant, nursing or if symptoms worsen or persist for more than a few days

KEEP OUT OF REACH OF CHILDREN SECTION

Keep out of reach of children.